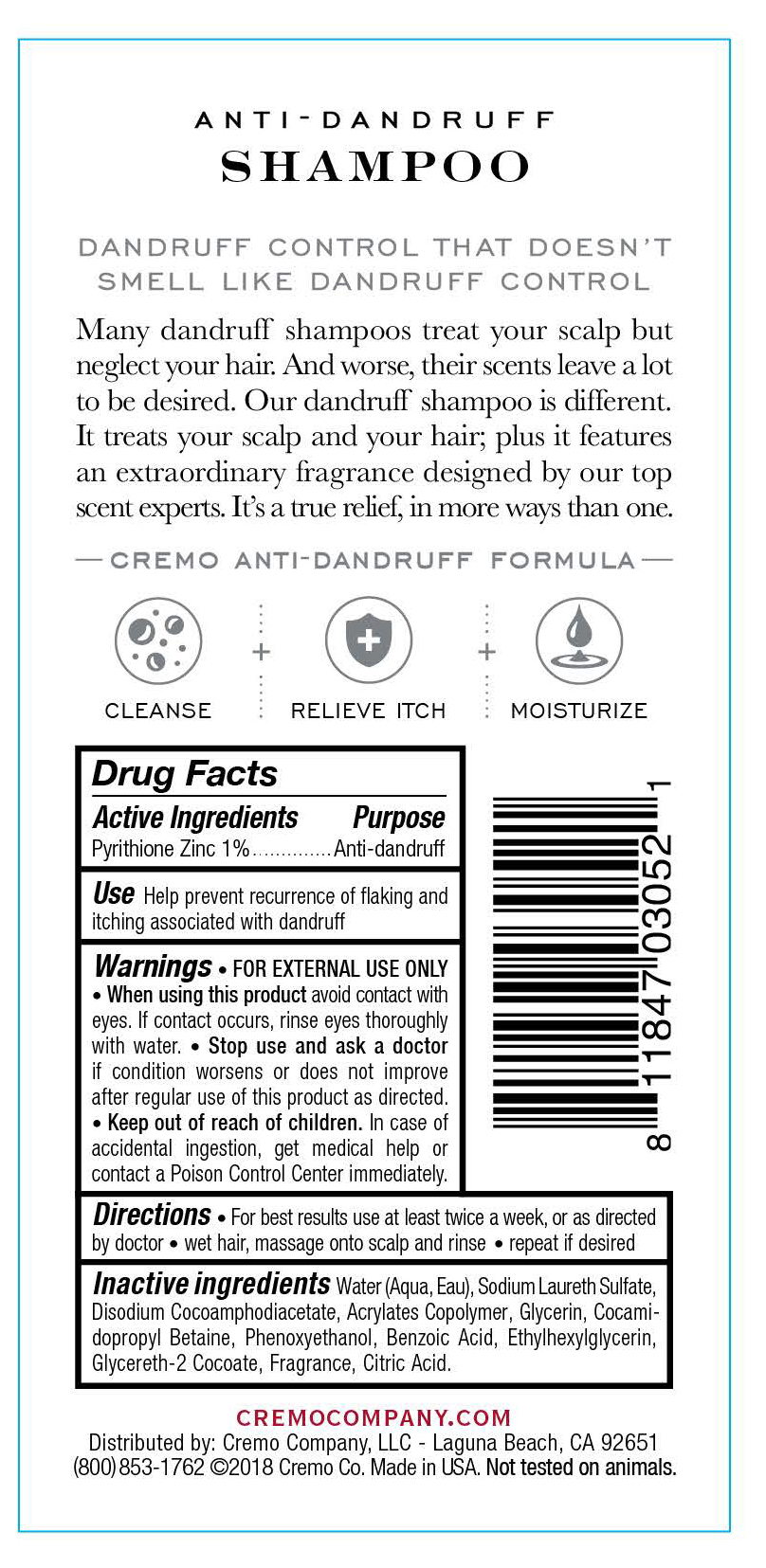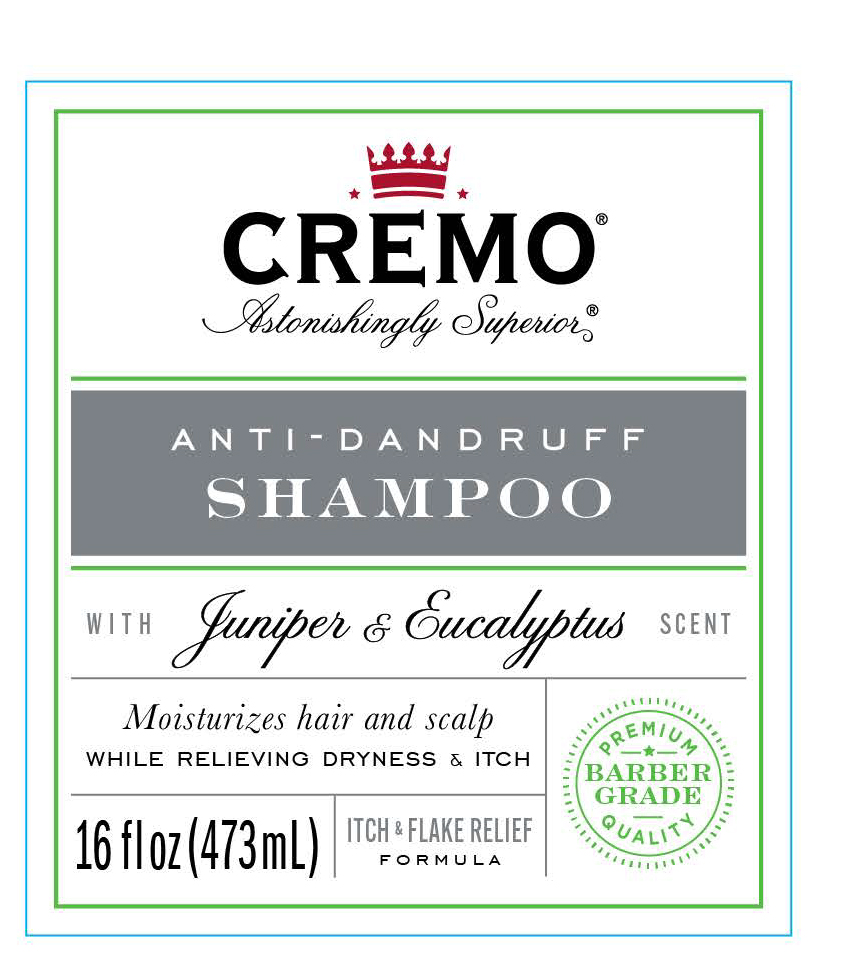 DRUG LABEL: Anti-Dandruff Juniper and Eucalyptus
NDC: 71825-105 | Form: SHAMPOO
Manufacturer: Cremo company
Category: otc | Type: HUMAN OTC DRUG LABEL
Date: 20190115

ACTIVE INGREDIENTS: PYRITHIONE ZINC 1 g/100 mL
INACTIVE INGREDIENTS: WATER; DISODIUM COCOAMPHODIACETATE; GLYCERIN; BENZOIC ACID; ETHYLHEXYLGLYCERIN; CITRIC ACID MONOHYDRATE; BUTYL ACRYLATE/METHYL METHACRYLATE/METHACRYLIC ACID COPOLYMER (18000 MW); COCAMIDOPROPYL BETAINE; GLYCERETH-2 COCOATE; SODIUM LAURETH SULFATE

Cremo Anti-Dandruff Shampoo Juniper and Eucalyptus

Active ingredients Purpose

Pyrithione Zinc 1% Anti-Dandruff

PURPOSE

Use Help prevent reccurence of flaking and itching associated with dandruff

Keep out of reach of children. In case of accidental ingestion, get medical help or contact a Posion Control Center immediately.

Stop use and ask a doctor if condition worsens or does not improve after regular use of this product as directed.

Warnings

· FOR EXTERNAL USE ONLY

· When using this product, avoid contact with eyes. If contact occurs, rinse eyes thoroughly with water

Directions

· For best results, use at least twice a week, or as directed by a doctor

· Wet hair, massage onto scalp and rinse

· repeat if desired

INACTIVE INGREDIENT

Water(aqua, Eau), Sodium Laureth Sulfate, Disodium Cocoamphodiacetate, Acrylates Copolymer, Glycerin, Cocamidopropyl Betaine, Phenoxyethanol, Benzoic Acid, Ethylhexylglycerin, glycereth-2 Cocoate, Fragrance, Citric Acid.

PACKAGE LABEL

Cremo

Anti-Dandruff Shampoo

Itch & Flake Relief Formula

Moisturizes Hair and scalp while relieving dryness and itch

Juniper & Eucalyptus

16 fl oz 473 mL